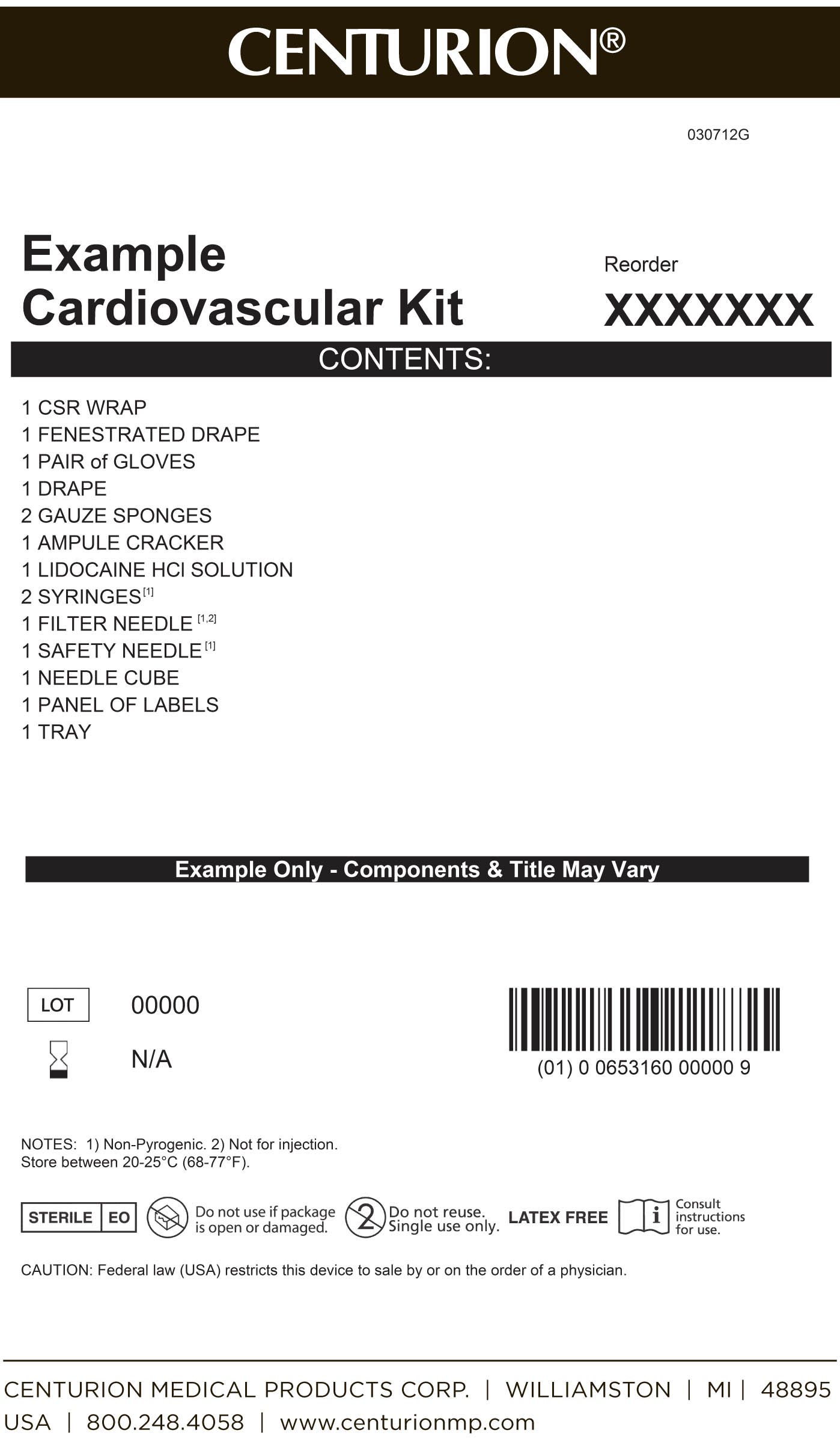 DRUG LABEL: Cardiovascular Procedure Kit
NDC: 24840-1106 | Form: KIT | Route: INFILTRATION
Manufacturer: Centurion Medical Products
Category: other | Type: MEDICAL DEVICE
Date: 20120315

ACTIVE INGREDIENTS: LIDOCAINE HYDROCHLORIDE 20 mg/1 mL
INACTIVE INGREDIENTS: SODIUM CHLORIDE 6 mg/1 mL; METHYLPARABEN 1 mg/1 mL; SODIUM HYDROXIDE; HYDROCHLORIC ACID

Cardiovascular Procedure Kit

Cardiovascular Procedure Kit - Primary Label

MM1

DESCRIPTION

Xylocaine (lidocaine HCl) Injections are sterile, nonpyrogenic, aqueous solutions that contain a local anesthetic agent with or without epinephrine and are administered parenterally by injection.

Xylocaine solutions contain lidocaine HCl, which is chemically designated as acetamide, 2-(diethylamino)-N-(2,6-dimethylphenyl)-, monohydrochloride and has the molecular wt. 270.8.

Epinephrine is (-) -3, 4-Dihydroxy-α-[(methylamino) methyl] benzyl alcohol and has the molecular wt. 183.21.

Xylocaine MPF is a sterile, nonpyrogenic, isotonic solution containing sodium chloride. Xylocaine in multiple dose vials: Each mL also contains 1 mg methylparaben as antiseptic preservative. The pH of these solutions is adjusted to approximately 6.5 (5.0 to 7.0) with sodium hydroxide and/or hydrochloric acid.

Xylocaine MPF with Epinephrine is a sterile, nonpyrogenic, isotonic solution containing sodium chloride. Each mL contains lidocaine hydrochloride and epinephrine, with 0.5 mg sodium metabisulfite as an antioxidant and 0.2 mg citric acid as a stabilizer. Xylocaine with Epinephrine in multiple dose vials: Each mL also contains 1 mg methylparaben as antiseptic preservative. The pH of these solutions is adjusted to approximately 4.5 (3.3 to 5.5) with sodium hydroxide and/or hydrochloric acid.